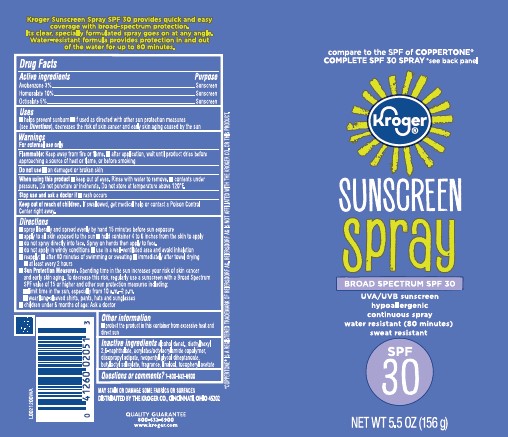 DRUG LABEL: Sport Sunscreen SPF 50
NDC: 59450-956 | Form: SPRAY
Manufacturer: The Kroger Co.
Category: otc | Type: HUMAN OTC DRUG LABEL
Date: 20260227

ACTIVE INGREDIENTS: AVOBENZONE 30 mg/1 g; HOMOSALATE 100 mg/1 g; OCTISALATE 50 mg/1 g
INACTIVE INGREDIENTS: ALCOHOL; DIETHYLHEXYL 2,6-NAPHTHALATE; ACRYLATE/ISOBUTYL METHACRYLATE/N-TERT-OCTYLACRYLAMIDE COPOLYMER (40000 MW); DIISOPROPYL ADIPATE; NEOPENTYL GLYCOL DIHEPTANOATE; BUTYLOCTYL SALICYLATE; LINALOOL, (+/-)-; .ALPHA.-TOCOPHEROL ACETATE

Kroger D56.000/D56AA
Moisturizing Sunscreen Spray SPF 30

Claims

Kroger Sport Sunscreen Spray 30 provides quick and easy coverage with broad-spectrum protection. Its clear, specially formulated spray goes on at any angle. Water-resistant formula provides protection in and out of the water for up to 80 minutes.

Active Ingredients

Avobenzone 3%

Homosalate 10%

Octisalate 5%

Purpose

Sunscreen

Uses

- helps prevent sunburn
- if used as directed with other sun protection measures (see Directions), decreases the risk of skin cancer and early skin aging caused by the sun

Warnings

For external use only

Flammable

- Flammable: keep away from fire or flame.
- After application, wait until product dries before approaching a source of heat or flame, or before smoking

Do not use

on damaged or broken skin

When using this product

- keep out of eyes. Rinse with water to remove.
- contents under pressure. Do not puncture or incinerate. Do not store at temperature above 120°F.

Stop use and ask a doctor if

- rash occurs

Keep out of reach of children.

If swallowed, seek immediate medical attention or call a poison control center right away.

Directions

- spray liberally and spread evenly by hand 15 minutes before sun exposure
- apply to all skin exposed to the sun
- hold container 4 to 6 inches from the skin to apply
- do not spray directly into face. Spray on hands then apply to face.
- do not apply in windy conditions
- use in a well-ventilated area and avoid inhalation
- reapply:
- after 80 minutes of swimming or sweating
- immediately after towel drying
- at least every 2 hours
- Sun Protection Measures.Spending time in the sun increases your risk of skin cancer and early skin aging. To decrease this risk, regularly use a sunscreen with a Broad Spectrum SPF value of 15 or higher and other sun protection measures including:
- limit time in the sun, especially from 10 a.m.–2 p.m.
- wear long-sleeved shirts, pants, hats and sunglasses
- children under 6 months of age: Ask a doctor

Other information

protect the product in this container from excessive heat and direct sun

Inactive ingredients

alcohol denat., diethylhexyl 2,6-naphthalate, acrylates/octylacrylamide copolymer, diisopropyl adipate, neopentyl glycol diheptanoate, butyloctyl salicylate, fragrance, linalool, tocopheryl acetate

Questions or comments?

1-800-632-6900

Disclaimers

May stain or damage some fabrics or surfaces

*COPPERTONEIS A REGISTERED TRADEMARK OF BEIERSDORF AG. BEIERSDORF AGIS NOT AFFILIATED WITH THE KROGER CO. OR THIS PRODUCT.

Adverse Reaction

DISTRIBUTED BY THE KROGER CO., CINCINNATI, OHIO 45202

QUALITY GUARANTEE

800-632-6900

www.kroger.com

Principal display panel

compare to THE SPF of COPPERTONE® COMPLETE SPF 30 SPRAY*see back panel

Kroger®

SUNSCREEN SPRAY

BROAD SPECTRUM SPF 50

UVA/UVB sunscreen

hypoallergenic

continuous spray

water resistant (80 minutes)

sweat resistant

SPF 30

NET WT 5.5 OZ (156 g)